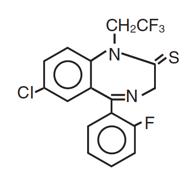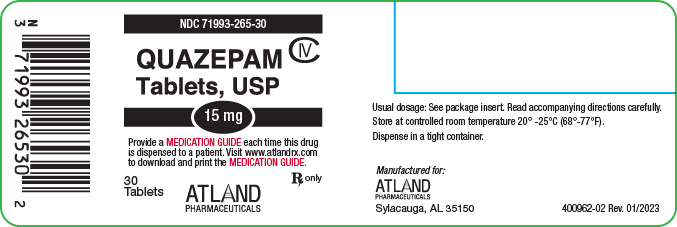 DRUG LABEL: Quazepam
NDC: 71993-265 | Form: TABLET
Manufacturer: Atland Pharmaceuticals, LLC
Category: prescription | Type: HUMAN PRESCRIPTION DRUG LABEL
Date: 20251023
DEA Schedule: CIV

ACTIVE INGREDIENTS: QUAZEPAM 15 mg/1 1
INACTIVE INGREDIENTS: POWDERED CELLULOSE; STARCH, CORN; FD&C YELLOW NO. 6; LACTOSE; MAGNESIUM STEARATE; SILICON DIOXIDE; SODIUM LAURYL SULFATE

HIGHLIGHTS OF PRESCRIBING INFORMATION

These highlights do not include all the information needed to use QUAZEPAM TABLETS safely and effectively. See full prescribing information for QUAZEPAM TABLETS.
QUAZEPAM TABLETS for oral use C-IV
Initial U.S. Approval: 1985

WARNING: RISKS FROM CONCOMITANT USE WITH OPIOIDS; ABUSE, MISUSE, AND ADDICTION; and DEPENDENCE AND WITHDRAWAL REACTIONS

See full prescribing information for complete boxed warning.

- Concomitant use of benzodiazepines and opioids may result in profound sedation, respiratory depression, coma, and death. Reserve concomitant prescribing of these drugs for use in patients for whom alternative treatment options are inadequate. Limit dosages and durations to the minimum required.
- Follow patients for signs and symptoms of respiratory depression and sedation (5.1, 7).
- The use of benzodiazepines, including Quazepam Tablets, exposes users to risks of abuse, misuse, and addiction, which can lead to overdose or death. Before prescribing Quazepam Tablets and throughout treatment, assess each patient’s risk for abuse, misuse, and addiction (5.2).
- Abrupt discontinuation or rapid dosage reduction of Quazepam Tablets after continued use may precipitate acute withdrawal reactions, which can be life-threatening. To reduce the risk of withdrawal reactions, use a gradual taper to discontinue Quazepam Tablets or reduce the dosage (2.3, 5.3).

RECENT MAJOR CHANGES

Warnings and Precautions (5.9) | 01/2023

1 INDICATIONS AND USAGE

Quazepam Tablets, a gamma-aminobutyric (GABAA) agonist, is indicated for the treatment of insomnia characterized by difficulty falling asleep, frequent nocturnal awakenings, and/or early morning awakenings. (1)

2 DOSAGE AND ADMINISTRATION

Use the lowest dose effective for the patient:

- Recommended initial dose is 7.5 mg (2)
- Split the 15 mg tablet along the score line to achieve 7.5 mg dose (2)
- The elderly and debilitated may be more sensitive to benzodiazepines (2)

3 DOSAGE FORMS AND STRENGTHS

15 mg functionally scored tablet, oral (3)

4 CONTRAINDICATIONS

- Hypersensitivity to Quazepam Tablets or other benzodiazepines (4)
- Established or suspected sleep apnea, or chronic pulmonary insufficiency (4)

5 WARNINGS AND PRECAUTIONS

- CNS depressant effects: Impaired alertness and motor coordination, including risk of daytime impairment. Caution patients against driving and other activities requiring complete mental alertness (5.4)
- The failure of insomnia to remit after 7 to 10 days of treatment may indicate the presence of a primary psychiatric and/or medical illness that should be evaluated. (5.5)
- Severe anaphylactic/anaphylactoid reactions: Angioedema and anaphylaxis have been reported. Do not rechallenge if such reactions occur. (5.6)
- Sleep driving and other complex behaviors while not fully awake. Risk increases with dose and concomitant CNS depressants and alcohol. Immediately evaluate any new onset behavioral changes (5.7)
- Worsening of depression or suicidal thinking may occur: Prescribe the least number of tablets feasible to avoid intentional overdose (5.8)

6 ADVERSE REACTIONS

Most common adverse reactions (>1%): drowsiness, headache, fatigue, dizziness, dry mouth, dyspepsia (6.1)

To report SUSPECTED ADVERSE REACTIONS, contact Atland Pharmaceuticals at 1-844-416-4284 or FDA at 1-800-FDA-1088 or www.fda.gov/medwatch. (6)

7 DRUG INTERACTIONS

- CNS Depressants: downward dose adjustment may be necessary due to additive effects (7)

FULL PRESCRIBING INFORMATION

WARNING: RISKS FROM CONCOMITANT USE WITH OPIOIDS; ABUSE, MISUSE, AND ADDICTION; and DEPENDENCE AND WITHDRAWAL REACTIONS

- Concomitant use of benzodiazepines and opioids may result in profound sedation, respiratory depression, coma, and death. Reserve concomitant prescribing of these drugs in patients for whom alternative treatment options are inadequate. Limit dosages and durations to the minimum required. Follow patients for signs and symptoms of respiratory depression and sedation [see Warnings and Precautions (5.1), Drug Interactions (7)] .
- The use of benzodiazepines, including Quazepam Tablets, exposes users to risks of abuse, misuse, and addiction, which can lead to overdose or death. Abuse and misuse of benzodiazepines commonly involve concomitant use of other medications, alcohol, and/or illicit substances, which is associated with an increased frequency of serious adverse outcomes. Before prescribing Quazepam Tablets and throughout treatment, assess each patient’s risk for abuse, misuse, and addiction [see Warnings and Precautions (5.2)] .
- The continued use of benzodiazepines, including Quazepam Tablets, may lead to clinically significant physical dependence. The risks of dependence and withdrawal increase with longer treatment duration and higher daily dose. Abrupt discontinuation or rapid dosage reduction of Quazepam Tablets after continued use may precipitate acute withdrawal reactions, which can be life-threatening. To reduce the risk of withdrawal reactions, use a gradual taper to discontinue Quazepam Tablets or reduce the dosage [see Dosage and Administration (2.3) and Warnings and Precautions (5.3)] .

1 INDICATIONS AND USAGE

Quazepam Tablets are indicated for the treatment of insomnia characterized by difficulty in falling asleep, frequent nocturnal awakenings, and/or early morning awakenings. The effectiveness of Quazepam Tablets has been established in placebo-controlled clinical studies of 5 nights duration in acute and chronic insomnia. The sustained effectiveness of Quazepam Tablets has been established in chronic insomnia in a sleep lab (polysomnographic) study of 28 nights duration. Because insomnia is often transient and intermittent, the prolonged administration of Quazepam Tablets is generally not necessary or recommended. Since insomnia may be a symptom of several other disorders, the possibility that the complaint may be related to a condition for which there is a more specific treatment should be considered.

2 DOSAGE AND ADMINISTRATION

2.1 Dosage Recommendations

Use the lowest dose effective for the patient, as important adverse effects of Quazepam Tablets are dose related. The recommended initial dose is 7.5 mg. The 7.5 mg dose can be increased to 15 mg if necessary for efficacy. The 7.5 mg dose can be achieved by splitting the 15 mg tablet along the score line.

2.2 Special Populations

Elderly and debilitated patients may be more sensitive to benzodiazepines.

2.3 Discontinuation or Dosage Reduction of Quazepam Tablets

To reduce the risk of withdrawal reactions, use a gradual taper to discontinue Quazepam Tablets or reduce the dosage. If a patient develops withdrawal reactions, consider pausing the taper or increasing the dosage to the previous tapered dosage level. Subsequently decrease the dosage more slowly [see Warnings and Precautions (5.3) and Drug Abuse and Dependence (9.3)] .

3 DOSAGE FORMS AND STRENGTHS

Tablets, 15 mg, functionally scored, capsule-shaped, light orange, slightly white speckled tablets, impressed with the product identification number 15 on one side of the tablet, and the product name (DORAL) on the other.

4 CONTRAINDICATIONS

Quazepam Tablets are contraindicated in patients with known hypersensitivity to quazepam or other benzodiazepines. Rare cases of angioedema involving the tongue, glottis or larynx have been reported in patients after taking the first or subsequent doses of Quazepam Tablets. Some patients have had additional symptoms such as dyspnea, throat closing, or nausea and vomiting that suggest anaphylaxis. Patients who develop such reactions should not be rechallenged with Quazepam Tablets.

Contraindicated in patients with established or suspected sleep apnea, or with pulmonary insufficiency.

5 WARNINGS AND PRECAUTIONS

5.1 Risks from Concomitant Use with Opioids

Concomitant use of benzodiazepines, including Quazepam Tablets, and opioids may result in profound sedation, respiratory depression, coma, and death. Because of these risks, reserve concomitant prescribing of these drugs in patients for whom alternative treatment options are inadequate.

Observational studies have demonstrated that concomitant use of opioid analgesics and benzodiazepines increases the risk of drug-related mortality compared to use of opioids alone. If a decision is made to prescribe Quazepam Tablets concomitantly with opioids, prescribe the lowest effective dosages and minimum durations of concomitant use, and follow patients closely for signs and symptoms of respiratory depression and sedation. In patients already receiving an opioid analgesic, prescribe a lower initial dose of Quazepam Tablets than indicated in the absence of an opioid and titrate based on clinical response. If an opioid is initiated in a patient already taking Quazepam Tablets, prescribe a lower initial dose of the opioid and titrate based upon clinical response.

Advise both patients and caregivers about the risks of respiratory depression and sedation when Quazepam Tablets is used with opioids. Advise patients not to drive or operate heavy machinery until the effects of concomitant use with the opioid have been determined. [see Drug Interactions (7)] .

5.2 Abuse, Misuse, and Addiction

The use of benzodiazepines, including Quazepam Tablets, exposes users to the risks of abuse, misuse, and addiction, which can lead to overdose or death. Abuse and misuse of benzodiazepines often (but not always) involve the use of doses greater than the maximum recommended dosage and commonly involve concomitant use of other medications, alcohol, and/or illicit substances, which is associated with an increased frequency of serious adverse outcomes, including respiratory depression, overdose, or death [see Drug Abuse and Dependence (9.2)] .

Before prescribing Quazepam Tablets and throughout treatment, assess each patient’s risk for abuse, misuse, and addiction (e.g., using a standardized screening tool). Use of Quazepam Tablets, particularly in patients at elevated risk, necessitates counseling about the risks and proper use of Quazepam Tablets along with monitoring for signs and symptoms of abuse, misuse, and addiction. Prescribe the lowest effective dosage; avoid or minimize concomitant use of CNS depressants and other substances associated with abuse, misuse, and addiction (e.g., opioid analgesics, stimulants); and advise patients on the proper disposal of unused drug. If a substance use disorder is suspected, evaluate the patient and institute (or refer them for) early treatment, as appropriate.

5.3 Dependence and Withdrawal Reactions

To reduce the risk of withdrawal reactions, use a gradual taper to discontinue Quazepam Tablets or reduce the dosage (a patient-specific plan should be used to taper the dose) [see Dosage and Administration (2.3)] .

Patients at an increased risk of withdrawal adverse reactions after benzodiazepine discontinuation or rapid dosage reduction include those who take higher dosages, and those who have had longer durations of use.

Acute Withdrawal Reactions
The continued use of benzodiazepines, including Quazepam Tablets, may lead to clinically significant physical dependence. Abrupt discontinuation or rapid dosage reduction of Quazepam Tablets after continued use, or administration of flumazenil (a benzodiazepine antagonist) may precipitate acute withdrawal reactions, which can be life-threatening (e.g., seizures) [see Drug Abuse and Dependence (9.3)] .

Protracted Withdrawal Syndrome
In some cases, benzodiazepine users have developed a protracted withdrawal syndrome with withdrawal symptoms lasting weeks to more than 12 months [see Drug Abuse and Dependence (9.3)] .

5.4 CNS-Depressant Effects and Daytime Impairment

Quazepam Tablet is a central nervous system (CNS) depressant and can impair daytime function in some patients even when used as prescribed. Prescribers should monitor for excess depressant effects, but impairment can occur in the absence of subjective symptoms, and may not be reliably detected by ordinary clinical exam (i.e. less than formal psychomotor testing). While pharmacodynamics tolerance or adaptation to some adverse depressant effects of Quazepam Tablets may develop, patients using Quazepam Tablets should be cautioned against driving or engaging in other hazardous activities or activities requiring complete mental alertness.

Additive effects occur with concomitant use of other CNS depressants (e.g., other benzodiazepines, opioids, tricyclic antidepressants, alcohol), including daytime use. Downward dose adjustment of Quazepam Tablets and concomitant CNS depressants should be considered. The potential for adverse drug interactions continues for several days following discontinuation of Quazepam Tablets, until serum levels of both active parent drug and psychoactive metabolites decline.

Use of Quazepam Tablets with other sedative-hypnotics is not recommended. Alcohol generally should not be used during treatment with Quazepam Tablets. The risk of next-day psychomotor impairment is increased if Quazepam Tablets is taken with less than a full night of sleep remaining (7 to 8 hours); if higher than the recommended dose is taken; if co-administered with other CNS depressants [see Dosage and Administration (2.1)] .

Because Quazepam Tablets can cause drowsiness and a decreased level of consciousness, patients particularly the elderly, are at higher risk of falls.

5.5 Need to Evaluate for Co-morbid Diagnoses

Because sleep disturbances may be the presenting manifestation of a physical and/or psychiatric disorder, symptomatic treatment of insomnia should be initiated only after a careful evaluation of the patient. The failure of insomnia to remit after 7 to 10 days of treatment may indicate the presence of a primary psychiatric and/or medical illness that should be evaluated. Worsening of insomnia or the emergence of new thinking or behavior abnormalities may be the consequence of an unrecognized psychiatric or physical disorder. Such findings have emerged during the course of treatment with sedative-hypnotic drugs.

5.6 Severe Anaphylactic and Anaphylactoid Reactions

Rare cases of angioedema involving the tongue, glottis or larynx have been reported in patients after taking the first or subsequent doses of sedative-hypnotics, including Quazepam Tablets. Some patients have had additional symptoms such as dyspnea, throat closing, or nausea and vomiting that suggest anaphylaxis.

Some patients have required medical therapy in the emergency department. If angioedema involves the tongue, glottis or larynx, airway obstruction may occur and be fatal. Patients who develop angioedema after treatment with Quazepam Tablets should not be rechallenged with the drug.

5.7 Abnormal Thinking and Behavior Changes

Abnormal thinking and behavior changes have been reported in patients treated with sedative-hypnotics including Quazepam Tablets. Some of these changes include decreased inhibition (e.g., aggressiveness and extroversion that seemed out of character), bizarre behavior, and depersonalization. Visual and auditory hallucinations have also been reported. Amnesia, and other neuro-psychiatric symptoms may occur.

Paradoxical reactions such as stimulation, agitation, increased muscle spasticity, and sleep disturbances may occur unpredictably.

Complex behaviors such as "sleep-driving" (i.e., driving while not fully awake, with amnesia for the event) have been reported with use of sedative-hypnotics. These behaviors can occur with initial treatment or in patients previously tolerant of Quazepam Tablets or other sedative-hypnotics. Although these behaviors can occur with use at therapeutic doses, risk is increased by higher doses or concomitant use of alcohol or other CNS depressants. Due to risk to the patient and community, Quazepam Tablets should be discontinued if "sleep-driving" occurs.

Other complex behaviors (e.g., preparing and eating food, making phone calls, or having sex) have been reported in patients who are not fully awake after taking a sedative-hypnotic. As with sleep-driving, patients usually do not remember these events.

5.8 Worsening of Depression

Benzodiazepines may worsen depression. Consequently, appropriate precautions (e.g., limiting the total prescription size and increased monitoring for suicidal ideation) should be considered.

5.9 Neonatal Sedation and Withdrawal Syndrome

Use of Quazepam Tablets late in pregnancy can result in sedation (respiratory depression, lethargy, hypotonia) and/or withdrawal symptoms (hyperreflexia, irritability, restlessness, tremors, inconsolable crying, and feeding difficulties) in the neonate [see Use in Specific Populations (8.1)] . Monitor neonates exposed to Quazepam Tablets during pregnancy or labor for signs of sedation and monitor neonates exposed to Quazepam Tablets during pregnancy for signs of withdrawal; manage these infants accordingly.

6 ADVERSE REACTIONS

The following serious adverse reactions are discussed in greater detail in other sections of the label:

- Risks from Concomitant Use with Opioids [see Warnings and Precautions (5.1)]
- Abuse, Misuse, and Addiction [see Warnings and Precautions (5.2)]
- Dependence and Withdrawal Reactions [see Warnings and Precautions (5.3)]
- CNS-depressant effects and next-day impairment [see Warnings and Precautions (5.4)]
- Abnormal thinking and behavior changes, and complex behaviors [see Warnings and Precautions (5.7)]
- Worsening of depression [see Warnings and Precautions (5.8)]
- Neonatal Sedation and Withdrawal Syndrome [see Warnings and Precautions (5.9)]

6.1 Clinical Trials Experience

Because clinical trials are conducted under widely varying conditions, adverse reaction rates observed in the clinical trials of a drug cannot be directly compared to rates in the clinical trials of another drug and may not reflect the rates observed in practice. The table shows adverse reactions occurring at an incidence of 1% or greater in relatively short-duration, placebo-controlled clinical trials of Quazepam Tablets.

 | Quazepam Tablets 15 mg | PLACEBO
NUMBER OF PATIENTS | 267 | 268
 | % OF PATIENTS REPORTING
Central Nervous System
Daytime Drowsiness | 12 | 3
Headache | 5 | 2
Fatigue | 2 | 0
Dizziness | 2 | <1
Autonomic Nervous System
Dry Mouth | 2 | <1
Gastrointestinal System
Dyspepsia | 1 | <1

A double-blind, controlled sleep laboratory study (N=30) in elderly patients compared the effects of Quazepam Tablets 7.5 mg and 15 mg to that of placebo over a period of 7 days. Both the 7.5 mg and 15 mg doses appeared to be well tolerated. Caution must be used in interpreting this data due to the small size of the study.

7 DRUG INTERACTIONS

The concomitant use of benzodiazepines and opioids increases the risk of respiratory depression because of actions at different receptor sites in the CNS that control respiration. Benzodiazepines interact at GABAA sites and opioids interact primarily at mu receptors. When benzodiazepines and opioids are combined, the potential for benzodiazepines to significantly worsen opioid-related respiratory depression exists. Limit dosage and duration of concomitant use of benzodiazepines and opioids, and monitor patients closely for respiratory depression and sedation.

Benzodiazepines, including Quazepam Tablets, produce additive CNS depressant effects when co-administered with ethanol or other CNS depressants (e.g. psychotropic medications, anticonvulsants, antihistamines). Downward dose adjustment of Quazepam Tablets and/or concomitant CNS depressants may be necessary because of additive effects.

8 USE IN SPECIFIC POPULATIONS

8.1 Pregnancy

Pregnancy Exposure Registry
There is a pregnancy registry that monitors pregnancy outcomes in women exposed to psychiatric medications, including Quazepam Tablets, during pregnancy. Healthcare providers are encouraged to register patients by calling the National Pregnancy Registry for Psychiatric Medications at 1-866-961-2388 or visiting on line at https://womensmentalhealth.org/pregnancyregistry/.

Risk Summary
Infants born to mothers using benzodiazepines late in pregnancy have been reported to experience symptoms of sedation and/or neonatal withdrawal [see Warnings and Precautions (5.9) and Clinical Considerations] . Available data from published observational studies of pregnant women exposed to benzodiazepines do not report a clear association with benzodiazepines and major birth defects (see Data).

The background risk of major birth defects and miscarriage for the indicated population is unknown. All pregnancies have a background risk of birth defect, loss, or other adverse outcomes. In the U.S. general population, the estimated risk of major birth defects and of miscarriage in clinically recognized pregnancies is 2% to 4% and 15% to 20%, respectively.

Clinical Considerations
Fetal/Neonatal Adverse Reactions
Benzodiazepines cross the placenta and may produce respiratory depression, hypotonia, and sedation in neonates. Monitor neonates exposed to Quazepam Tablets during pregnancy or labor for signs of sedation, respiratory depression, hypotonia, and feeding problems. Monitor neonates exposed to Quazepam Tablets during pregnancy for signs of withdrawal. Manage these neonates accordingly [see Warnings and Precautions (5.9)] .

Data
Human Data
Published data from observational studies on the use of benzodiazepines during pregnancy do not report a clear association with benzodiazepines and major birth defects. Although early studies reported an increased risk of congenital malformations with diazepam and chlordiazepoxide, there was no consistent pattern noted. In addition, the majority of more recent case-control and cohort studies of benzodiazepine use during pregnancy, which were adjusted for confounding exposures to alcohol, tobacco and other medications, have not confirmed these findings.

Animal Data
Developmental toxicity studies of Quazepam Tablets in mice at doses up to 400 times the human dose (15 mg) revealed no major drug-related malformations. Minor fetal skeletal variations that occurred were delayed ossification of the sternum, vertebrae, distal phalanges and supraoccipital bones, at doses approximately 70 and 400 times the human dose. A developmental toxicity study of Quazepam Tablets in New Zealand rabbits at doses up to approximately 130 times the human dose demonstrated no effect on fetal morphology or development of offspring.

8.3 Nursing Mothers

Risk Summary

Quazepam and its metabolites are present in breast milk. There are reports of sedation, poor feeding and poor weight gain in infants exposed to benzodiazepines through breast milk. The effects of quazepam on milk production are unknown. The developmental and health benefits of breastfeeding should be considered along with the mother's clinical need for Quazepam Tablets and any potential adverse effects on the breastfed infant from Quazepam Tablets or from the underlying maternal condition.

Clinical Considerations
Infants exposed to Quazepam Tablets through breast milk should be monitored for sedation, poor feeding and poor weight gain.

8.4 Pediatric Use

Safety and effectiveness in pediatric patients have not been established.

8.5 Geriatric Use

Quazepam Tablets may cause confusion and over-sedation in the elderly. Elderly patients generally should be started on a low dose of Quazepam Tablets and observed closely. Elderly and debilitated patients may be more sensitive to benzodiazepines, reflecting the greater frequency of decreased hepatic, renal, or cardiac function, and of concomitant disease or other drug therapy. A double-blind controlled sleep laboratory study (N=30) compared the effects of Quazepam Tablets 7.5 mg and 15 mg to that of placebo over a period of 7 days. Both the 7.5 mg and 15 mg doses appeared to be well tolerated. Caution must be used in interpreting this data due to the small size of the study.

9 DRUG ABUSE AND DEPENDENCE

9.1 Controlled Substance

Quazepam Tablets contain quazepam, a Schedule IV controlled substance.

9.2 Abuse

Quazepam Tablet is a benzodiazepine and a CNS depressant with a potential for abuse and addiction. Abuse is the intentional, nontherapeutic use of a drug, even once, for its desirable psychological or physiological effects. Misuse is the intentional use, for therapeutic purposes, of a drug by an individual in a way other than prescribed by a health care provider or for whom it was not prescribed. Drug addiction is a cluster of behavioral, cognitive, and physiological phenomena that may include a strong desire to take the drug, difficulties in controlling drug use (e.g., continuing drug use despite harmful consequences, giving a higher priority to drug use than other activities and obligations), and possible tolerance or physical dependence. Even taking benzodiazepines as prescribed may put patients at risk for abuse and misuse of their medication. Abuse and misuse of benzodiazepines may lead to addiction.

Abuse and misuse of benzodiazepines often (but not always) involve the use of doses greater than the maximum recommended dosage and commonly involve concomitant use of other medications, alcohol, and/or illicit substances, which is associated with an increased frequency of serious adverse outcomes, including respiratory depression, overdose, or death. Benzodiazepines are often sought by individuals who abuse drugs and other substances, and by individuals with addictive disorders [see Warnings and Precautions (5.2)] .

The following adverse reactions have occurred with benzodiazepine abuse and/or misuse: abdominal pain, amnesia, anorexia, anxiety, aggression, ataxia, blurred vision, confusion, depression, disinhibition, disorientation, dizziness, euphoria, impaired concentration and memory, indigestion, irritability, muscle pain, slurred speech, tremors, and vertigo.

The following severe adverse reactions have occurred with benzodiazepine abuse and/or misuse: delirium, paranoia, suicidal ideation and behavior, seizures, coma, breathing difficulty, and death. Death is more often associated with polysubstance use (especially benzodiazepines with other CNS depressants such as opioids and alcohol).

9.3 Dependence

Physical Dependence
Quazepam Tablets may produce physical dependence from continued therapy. Physical dependence is a state that develops as a result of physiological adaptation in response to repeated drug use, manifested by withdrawal signs and symptoms after abrupt discontinuation or a significant dose reduction of a drug. Abrupt discontinuation or rapid dosage reduction of benzodiazepines or administration of flumazenil, a benzodiazepine antagonist, may precipitate acute withdrawal reactions, including seizures, which can be life-threatening. Patients at an increased risk of withdrawal adverse reactions after benzodiazepine discontinuation or rapid dosage reduction include those who take higher dosages (i.e., higher and/or more frequent doses) and those who have had longer durations of use [see Warnings and Precautions (5.3)] .

To reduce the risk of withdrawal reactions, use a gradual taper to discontinue Quazepam Tablets or reduce the dosage [see Dosage and Administration (2.3) and Warnings and Precautions (5.3)] .

Acute Withdrawal Signs and Symptoms
Acute withdrawal signs and symptoms have included abnormal involuntary movements, anxiety, blurred vision, depersonalization, depression, derealization, dizziness, fatigue, gastrointestinal adverse reactions (e.g., nausea, vomiting, diarrhea, weight loss, decreased appetite), headache, hyperacusis, hypertension, irritability, insomnia, memory impairment, muscle pain and stiffness, panic attacks, photophobia, restlessness, tachycardia, and tremor. More severe acute withdrawal signs and symptoms, including life-threatening reactions, have included catatonia, convulsions, delirium tremens, depression, hallucinations, mania, psychosis, and suicidality.

Protracted Withdrawal Syndrome
Protracted withdrawal syndrome associated with benzodiazepines is characterized by anxiety, cognitive impairment, depression, insomnia, formication, motor symptoms (e.g., weakness, tremor, muscle twitches), paresthesia, and tinnitus that persists beyond 4 to 6 weeks after initial benzodiazepine withdrawal. Protracted withdrawal symptoms may last weeks to more than 12 months. As a result, there may be difficulty in differentiating withdrawal symptoms from potential re-emergence or continuation of symptoms for which the benzodiazepine was being used.

Tolerance
Tolerance to Quazepam Tablets may develop from continued therapy. Tolerance is a physiological state characterized by a reduced response to a drug after repeated administration (i.e., a higher dose of a drug is required to produce the same effect that was once obtained at a lower dose). Tolerance may develop within days or weeks of the therapeutic effects of Quazepam Tablets; however, little tolerance develops to the amnestic reactions and other cognitive impairments caused by benzodiazepines.

10 OVERDOSAGE

Overdosage of benzodiazepines is characterized by central nervous system depression ranging from drowsiness to coma. In mild to moderate cases, symptoms can include drowsiness, confusion, dysarthia, lethargy, hypnotic state, diminished reflexes, ataxia, and hypotonia. Rarely, paradoxical or disinhibitory reactions (including agitation, irritability, impulsivity, violent behavior, confusion, restlessness, excitement, and talkativeness) may occur. In severe overdosage cases, patients may develop respiratory depression and coma. Overdosage of benzodiazepines in combination with other CNS depressants (including alcohol and opioids) may be fatal [see Warnings and Precautions (5.2)] . Markedly abnormal (lowered or elevated) blood pressure, heart rate, or respiratory rate raise the concern that additional drugs and/or alcohol are involved in the overdosage.

In managing benzodiazepine overdosage, employ general supportive measures, including intravenous fluids and airway management. Flumazenil, a specific benzodiazepine receptor antagonist indicated for the complete or partial reversal of the sedative effects of benzodiazepines in the management of benzodiazepine overdosage, can lead to withdrawal and adverse reactions, including seizures, particularly in the context of mixed overdosage with drugs that increase seizure risk (e.g., tricyclic and tetracyclic antidepressants) and in patients with long-term benzodiazepine use and physical dependency. The risk of withdrawal seizures with flumazenil use may be increased in patients with epilepsy. Flumazenil is contraindicated in patients who have received a benzodiazepine for control of a potentially life-threatening condition (e.g., status epilepticus). If the decision is made to use flumazenil, it should be used as an adjunct to, not as a substitute for, supportive management of benzodiazepine overdosage. See the flumazenil injection Prescribing Information.

Consider contacting a poison center (1-800-222-1222) or medical toxicologist for additional overdosage management recommendations.

11 DESCRIPTION

Quazepam Tablets contain quazepam, a trifluoroethyl benzodiazepine hypnotic agent, having the chemical name 7-chloro-5- (o-fluoro-phenyl)-1,3-dihydro-1-(2,2,2- trifluoroethyl)-2H-1,4-benzodiazepine-2-thione and the following structural

Quazepam has the empirical formula C17H11ClF4N2S, and a molecular weight of 386.8. It is a white crystalline compound, soluble in ethanol and insoluble in water.

Each Quazepam Tablet contains 15 mg of quazepam. The inactive ingredients for Quazepam Tablets include cellulose, corn starch, FD&C Yellow No. 6, lactose, magnesium stearate, silicon dioxide, and sodium lauryl sulfate.

12 CLINICAL PHARMACOLOGY

12.1 Mechanism of Action

Quazepam Tablet, like other central nervous system agents of the 14-benzodiazepine class, presumably exerts its effects by binding to stereo-specific receptors at several sites within the central nervous system (CNS). The exact mechanism of action is unknown.

12.3 Pharmacokinetics

Absorption

Quazepam Tablet is rapidly (absorption half-life of about 30 minutes) and well absorbed from the gastrointestinal tract. The peak plasma concentration of quazepam is approximately 20 ng/mL after a 15 mg dose and occurs at about 2 hours.

Metabolism

Quazepam, the active parent compound, is extensively metabolized in the liver; two of the plasma metabolites are 2-oxoquazepam and N-desalkyl-2-oxoquazepam. All three compounds show CNS depressant activity.

Distribution

The degree of plasma protein binding for quazepam and its two major metabolites is greater than 95%.

Elimination

Following administration of 14C-quazepam, 31% of the dose appeared in the urine and 23% in the feces over five days; only trace amounts of unchanged drug were present in the urine.

The mean elimination half-life of quazepam and 2-oxoquazepam is 39 hours and that of N-desalkyl-2-oxoquazepam is 73 hours. Steady-state levels of quazepam and 2-oxoquazepam are attained by the seventh daily dose and that of N-desalkyl-2-oxoquazepam by the thirteenth daily dose.

Special Populations

Geriatrics: The pharmacokinetics of quazepam and 2-oxoquazepam in geriatric subjects are comparable to those seen in young adults; as with desalkyl metabolites of other benzodiazepines, the elimination half-life of N-desalkyl-2-oxoquazepam in geriatric patients is about twice that of young adults.

Drug Interactions

Bupropion (a CYP2B6 substrate): Co-administration of a single dose of 150 mg Bupropion Hydrochloride XL with steady state quazepam did not significantly affect the AUC and Cmax of bupropion or its primary metabolite, hydroxybupropion.

13 NONCLINICAL TOXICOLOGY

13.1 Carcinogenesis, Mutagenesis, Impairment of Fertility

Carcinogenesis

Quazepam Tablet showed no evidence of carcinogenicity in oral carcinogenicity studies in mice and hamsters.

Mutagenesis

Quazepam Tablet was negative in the bacterial reverse mutation (Ames) assay and equivocal in the mouse lymphoma tk assay.

Impairment of Fertility

Reproduction studies in mice conducted with Quazepam Tablets at doses equal to 60 and

180 times the human dose of 15 mg produced slight reductions in fertility rate. Similar reductions in fertility rate have been reported in mice dosed with other benzodiazepines, and is believed to be related to the sedative effects of these drugs at high doses

14 CLINICAL STUDIES

The effectiveness of Quazepam Tablets was established in placebo-controlled clinical studies of 5 nights duration in acute and chronic insomnia. The sustained effectiveness of Quazepam Tablets was established in chronic insomnia in a sleep laboratory (polysomnographic) study of 28 nights duration. In the sleep laboratory study, Quazepam Tablets significantly decreased sleep latency and total wake time, and significantly increased total sleep time and percent sleep time, for one or more nights.

Quazepam Tablets 15 mg was effective on the first night of administration. Sleep latency, total wake time and wake time after sleep onset were still decreased and percent sleep time was still increased for several nights after the drug was discontinued. Percent slow wave sleep was decreased, and REM sleep was essentially unchanged. No transient sleep disturbance, such as “rebound insomnia,” was observed after withdrawal of the drug in sleep laboratory studies in 12 patients using 15 mg doses.

A double-blind, controlled sleep laboratory study (N=30) in elderly patients compared the effects of Quazepam Tablets 7.5 mg and 15 mg to that of placebo over a period of 7 days. Both the 7.5 mg and 15 mg doses appeared to be effective. Caution must be used in interpreting this data due to the small size of the study.

16 HOW SUPPLIED / STORAGE AND HANDLING

Quazepam Tablets, 15 mg, functionally scored, capsule-shaped, light orange, slightly white speckled tablets, impressed with the product identification number 15 on one side of the tablet, and the product name (DORAL) on the other.

15 mg | Bottles of 30 | NDC 71993-265-30

Store Quazepam Tablets at controlled room temperature 20°-25°C (68°-77°F).

17 PATIENT COUNSELING INFORMATION

Advise the patient to read the FDA-approved patient labeling (Medication Guide).

Risks from Concomitant Use with Opioids
Inform patients and caregivers that potentially fatal additive effects may occur if Quazepam Tablets is used with opioids and not to use such drugs concomitantly unless supervised by a healthcare provider [see Warnings and Precautions (5.1), Drug Interactions (7)]

Abuse, Misuse, and Addiction
Inform patients that the use of Quazepam Tablets even at recommended dosages, exposes users to risks of abuse, misuse, and addiction, which can lead to overdose and death, especially when used in combination with other medications (e.g., opioid analgesics), alcohol, and/or illicit substances. Inform patients about the signs and symptoms of benzodiazepine abuse, misuse, and addiction; to seek medical help if they develop these signs and/or symptoms; and on the proper disposal of unused drug [see Warnings and Precautions (5.2) and Drug Abuse and Dependence (9.2)] .

Withdrawal Reactions
Inform patients that the continued use of Quazepam Tablets may lead to clinically significant physical dependence and that abrupt discontinuation or rapid dosage reduction of Quazepam Tablets may precipitate acute withdrawal reactions, which can be life-threatening. Inform patients that in some cases, patients have developed a protracted withdrawal syndrome with withdrawal symptoms lasting weeks to more than 12 months. Instruct patients that discontinuation or dosage reduction of Quazepam Tablets may require a slow taper [see Warnings and Precautions (5.3) and Drug Abuse and Dependence (9.3)] .

CNS Depressant Effects and Next-Day Impairment
Tell patients that Quazepam Tablets can cause next-day impairment, even in the absence of symptoms. Caution patients against driving or engaging in other hazardous activities or activities requiring complete mental alertness when using Quazepam Tablets. Tell patients that daytime impairment may persist for several days following discontinuation of Quazepam Tablets. Advise patients that increased drowsiness and decreased consciousness may increase the risk of falls in some patients [see Warnings and Precautions (5.4)]

Severe Allergic Reactions
Inform patients that severe allergic reactions can occur from Quazepam Tablets. Describe the signs/symptoms of these reactions and advise patients to seek medical attention immediately if these occur [see Warnings and Precautions (5.6)] .

Abnormal Thinking and Behavior Change
Instruct patients that sedative hypnotics can cause abnormal thinking and behavior change, including “sleep-driving” and other complex behaviors while not being fully awake (preparing and eating food, making phone calls, or having sex). Tell patients to call you immediately if they develop any of these symptoms [see Warnings and Precautions (5.7)] .

Suicide
Tell patients that Quazepam Tablets can worsen depression, and to immediately report any suicidal thoughts [see Warnings and Precautions (5.8)] .

Alcohol and Other Drugs
Ask patients about alcohol consumption, medicines they are taking now, and drugs they may be taking without a prescription. Advise patients that alcohol generally should not be used during treatment with Quazepam Tablets.

Pregnancy
Advise pregnant females that use of Quazepam Tablets late in pregnancy can result in sedation (respiratory depression, lethargy, hypotonia) and/or withdrawal symptoms (hyperreflexia, irritability, restlessness, tremors, inconsolable crying, and feeding difficulties) in newborns [see Warnings and Precautions (5.9), Use in Specific Populations (8.1)] . Instruct patients to inform their healthcare provider if they are pregnant.

Advise patients that there is a pregnancy exposure registry that monitors pregnancy outcomes in women exposed to Quazepam Tablets during pregnancy [see Use in Specific Populations (8.1)] .

Nursing
Instruct patients to notify their healthcare provider if they are breastfeeding or intend to breastfeed. Instruct breastfeeding patients using Quazepam Tablets to monitor infants for excessive sedation, poor feeding and poor weight gain, and to seek medical attention if they notice these signs [see Use in Specific Populations (8.3)] .

Galt Pharmaceuticals, LLC.
Atlanta, GA 30339

Printed in USA. 500495-09 Rev. 01/2023

Medication Guide
QUAZEPAM tablets, C-IV

What is the most important information I should know about Quazepam Tablets?

- Quazepam Tablets is a benzodiazepine medicine. Taking benzodiazepines with opioid medicines, alcohol, or other central nervous system (CNS) depressants (including street drugs) can cause severe drowsiness, breathing problems (respiratory depression), coma and death. Get emergency help right away if the following happens:
  - shallow or slowed breathing
  - breathing stops (which may lead to the heart stopping)
  - excessive sleepiness (sedation)

Do not drive or operate heavy machinery until you know how taking Quazepam Tablets with opioids affects you.

- Risk of abuse, misuse, and addiction.There is a risk of abuse, misuse, and addiction with benzodiazepines, including Quazepam Tablets which can lead to overdose and serious side effects including coma and death.
  - Serious side effects including coma and death have happened in people who have abused or misused benzodiazepines, including Quazepam Tablets. These serious side effects may include delirium, paranoia, suicidal thoughts or actions, seizures, and difficulty breathing. Call your healthcare provider or go to the nearest hospital emergency room right away if you get any of these serious side effects.
  - You can develop an addiction even if you take Quazepam Tablets as prescribed by your healthcare provider
  - Take Quazepam Tablets exactly as your healthcare provider prescribed.
  - Do not share your Quazepam Tablets with other people.
  - Keep Quazepam Tablets in a safe place and away from children.
- Physical dependence and withdrawal reactions.Quazepam Tablets can cause physical dependence and withdrawal reactions.
  - Do not suddenly stop taking Quazepam Tablets. Stopping Quazepam Tablets suddenly can cause serious and life-threatening side effects, including unusual movements, responses, or expressions, seizures, sudden and severe mental or nervous system changes, depression, seeing or hearing things that others do not see or hear, an extreme increase in activity or talking, losing touch with reality, and suicidal thoughts or actions. Call your healthcare provider or go to the nearest hospital emergency room right away if you get any of these symptoms.
  - Some people who stop benzodazepines have symptoms that can last for several weeks to more than 12 months, including, anxiety, trouble remembering, learning, or concentrating, depression, problems sleeping, feeling like insects are crawling under your skin, weakness, shaking, muscle twitching, burning or prickling feeling in your hands, arms, legs or feet, and ringing in your ears. Physical dependence is not the same as drug addiction. Your healthcare provider can tell you more about the differences between physical dependence and drug addiction.
  - Do not take more Quazepam Tablets than prescribed or take Quazepam Tablets for longer than prescribed.
- After taking Quazepam Tablets, you may get up out of bed while not being fully awake and do an activity that you do not know you are doing. The next morning, you may not remember that you did anything during the night. You have a higher chance for doing these activities if you drink alcohol or take other medicines that make you sleepy with Quazepam Tablets. Reported activities include:
  - driving a car (“sleep-driving”)
  - having sex
  - making and eating food
  - sleep-walking
  - talking on the phone

Call your healthcare provider right away if you find out that you have done any of the above activities after taking Quazepam Tablets.

What is Quazepam Tablets?

- Quazepam Tablets is a prescription medicine used to treat certain types of insomnia including difficulty falling asleep, waking up often during the night, or waking up early in the morning.
- Quazepam Tablets is a federal controlled substance (C-IV) because it contains quazepam that can be abused or lead to dependence. Keep Quazepam Tablets in a safe place to prevent misuse and abuse. Selling or giving away Quazepam Tablets may harm others, and is against the law. Tell your healthcare provider if you have ever abused or been dependent on alcohol, prescription medicines or street drugs.
- It is not known if Quazepam Tablets is safe and effective in children.

Do not take Quazepam Tablets if you:

- are allergic to quazepam or any of the ingredients in Quazepam Tablets. See the end of this Medication Guide for a complete list of ingredients in Quazepam Tablets.
- have had an allergic reaction to other sleep medicines or sedatives such as benzodiazepines. Symptoms of a serious allergic reaction can include:
  - swelling of your face, lips, and throat that may cause difficulty breathing or swallowing
  - nausea and vomiting
- have sleep apnea, breathing or lung problems

Before you take Quazepam Tablets, tell your healthcare provider about all of your medical conditions, including if you:

- have a history of depression, mental illness or, suicidal thoughts
- have a history of drug or alcohol abuse or addiction
- have lung disease or breathing problems
- are pregnant or plan to become pregnant.
  - Taking Quazepam Tablets late in pregnancy may cause your baby to have symptoms of sedation (breathing problems, sluggishness, low muscle tone), and/or withdrawal symptoms (jitteriness, irritability, restlessness, shaking, excessive crying, feeding problems).
  - Tell your healthcare provider right away if you become pregnant or think you are pregnant during treatment with Quazepam Tablets.
  - There is a pregnancy registry for women who take Quazepam Tablets during pregnancy. The purpose of the registry is to collect information about the health of you and your baby. If you become pregnant during treatment with Quazepam Tablets, talk to your healthcare provider about registering with the National Pregnancy Registry for Psychiatric Medications. You can register by calling 1-866-961-2388 or visiting https://womensmentalhealth.org/pregnancyregistry/.
- are breastfeeding, or plan to breastfeed. Quazepam Tablets can pass through your breast milk.
  - Breastfeeding during treatment with Quazepam Tablets may cause your baby to have sleepiness, feeding problems, and decreased weight gain.
  - Talk to your healthcare provider about the best way to feed your baby if you take Quazepam Tablets.

Tell your healthcare provider about all of the medicines you take, including prescription and over-the-counter medicines, vitamins, and herbal supplements.

Taking Quazepam Tablets with certain other medicines can cause side effects or affect how well Quazepam Tablets or the other medicines work.

Do not start or stop other medicines without talking to your healthcare provider.

Do not take Quazepam Tablets with other medicines that can make you sleepy unless your healthcare provider tells you to.

How should I take Quazepam Tablets?

- See “What is the most important information I should know about Quazepam Tablets?”
- Take Quazepam Tablets exactly as your healthcare providers tell you to take it.
- Quazepam Tablets comes in 15 mg tablets. Your healthcare provider may start your Quazepam Tablets dose at 7.5 mg which is half a tablet. Talk to your healthcare provider or pharmacist about your dose schedule.
- If you take too much Quazepam Tablets or overdose, get emergency treatment right away.

What are the possible side effects of Quazepam Tablets?

Quazepam Tablets may cause serious side effects, including:

- See “What is the most important information I should know about Quazepam Tablets?”
- Other conditions. Call your healthcare provider if your insomnia worsens or is not better within 7 to 10 days. This may mean that there is another condition causing your sleep problem.
- Severe allergic reactions. Symptoms include swelling of the tongue or throat, and trouble breathing. Other symptoms may include nausea and vomiting. Get emergency medical help right away if you have these symptoms after taking Quazepam Tablets.
- Abnormal thoughts and behavior. Symptoms include more outgoing or aggressive behavior than normal, confusion, agitation, hallucinations, worsening of depression, and suicidal thoughts.
- Quazepam Tablets can make you sleepy or dizzy and can slow your thinking and motor skills.
  - Do not drive, operate heavy machinery, or do other dangerous activities until you know how Quazepam Tablets affects you.
  - Do not drink alcohol or take other drugs that may make you sleepy or dizzy while taking Quazepam Tablets without first talking to your healthcare provider. When taken with alcohol or drugs that cause sleepiness or dizziness, Quazepam Tablets may make your sleepiness or dizziness much worse
- Depression. Pre-existing depression may emerge or worsen during use of benzodiazepines including Quazepam Tablets.

Call your healthcare provider right away if you have any of the above side effects while taking Quazepam Tablets. The most common side effects of Quazepam Tablets include:

- drowsiness
- headache
- feeling very tired
- dizziness
- dry mouth
- upset stomach

After you stop taking a sleep medicine, you may have symptoms for the next 1 to 2 days such as:

- trouble sleeping
- nausea
- flushing
- lightheadedness
- uncontrolled crying
- vomiting
- stomach cramps
- panic attack
- nervousness
- stomach area pain

These are not all the possible side effects of Quazepam Tablets. Call your doctor for medical advice about side effects. You may report side effects to FDA at 1-800-FDA-1088.

How should I store Quazepam Tablets?

- Store at room temperature between 68°F to 77°F (20°C to 25°C).
- Keep Quazepam Tablets and all medicines out of the reach of children.

General information about the safe and effective use of Quazepam Tablets.

Medicines are sometimes prescribed for purposes other than those listed in a Medication Guide. Do not use Quazepam Tablets for a condition for which it was not prescribed. Do not give Quazepam Tablets to other people, even if they have the same symptoms that you have. It may harm them. You can ask your healthcare provider or pharmacist for information about Quazepam Tablets that is written for healthcare professionals.

What are the ingredients in Quazepam Tablets?

Active Ingredient: quazepam

Inactive Ingredients: cellulose, corn starch, FD&C Yellow No.6, lactose, magnesium stearate, silicon dioxide, and sodium lauryl sulfate

Distributed by Atland Pharmaceuticals, Sylacauga, AL 35150 USA. If you would like more information, call Atland Pharmaceuticals at 1-855-965-2783 or visit www.atlandrx.com.

This Medication Guide has been approved by the U.S. Food and Drug Administration.

Revised: 01/2023

PACKAGE LABEL

PRINCIPAL DISPLAY PANEL

NDC 71993-265-30
Quazepam Tablets, USP
15 mg
30 Tablets
Rx Only